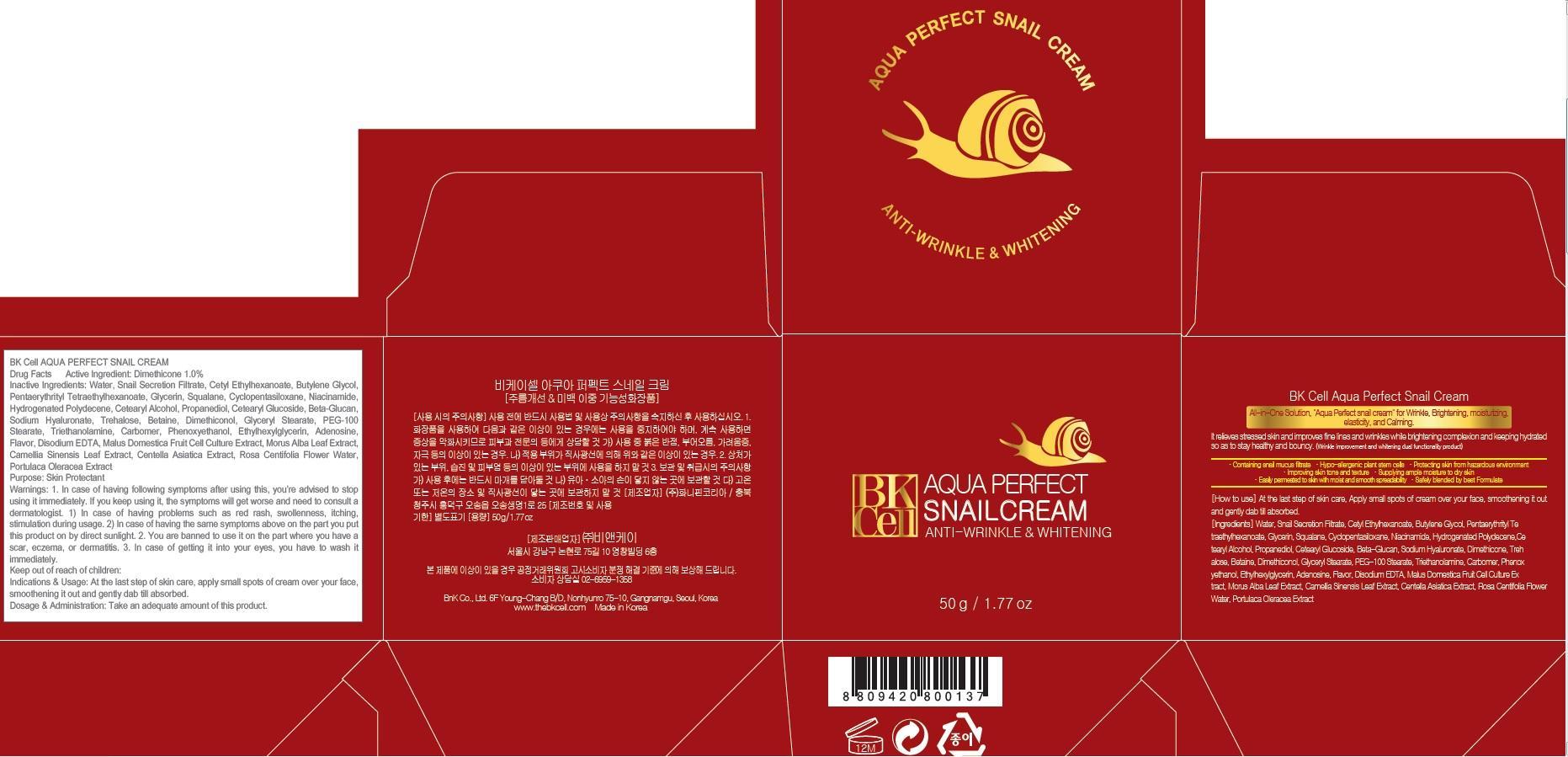 DRUG LABEL: BK Cell AQUA PERFECT SNAIL
NDC: 69946-060 | Form: CREAM
Manufacturer: BNK CO., LTD.
Category: otc | Type: HUMAN OTC DRUG LABEL
Date: 20150715

ACTIVE INGREDIENTS: Dimethicone 0.5 g/50 g
INACTIVE INGREDIENTS: Water; Cetyl Ethylhexanoate

ACTIVE INGREDIENT

Active Ingredient: Dimethicone 1.0%

INACTIVE INGREDIENT

Inactive Ingredients: Water, Snail Secretion Filtrate, Cetyl Ethylhexanoate, Butylene Glycol, Pentaerythrityl Tetraethylhexanoate, Glycerin, Squalane, Cyclopentasiloxane, Niacinamide, Hydrogenated Polydecene, Cetearyl Alcohol, Propanediol, Cetearyl Glucoside, Beta-Glucan, Sodium Hyaluronate, Trehalose, Betaine, Dimethiconol, Glyceryl Stearate, PEG-100 Stearate, Triethanolamine, Carbomer, Phenoxyethanol, Ethylhexylglycerin, Adenosine, Flavor, Disodium EDTA, Malus Domestica Fruit Cell Culture Extract, Morus Alba Leaf Extract, Camellia Sinensis Leaf Extract, Centella Asiatica Extract, Rosa Centifolia Flower Water, Portulaca Oleracea Extract

PURPOSE

Purpose: Skin Protectant

WARNINGS

Warnings: 1. In case of having following symptoms after using this, you're advised to stop using it immediately. If you keep using it, the symptoms will get worse and need to consult a dermatologist. 1) In case of having problems such as red rash, swollenness, itching, stimulation during usage. 2) In case of having the same symptoms above on the part you put this product on by direct sunlight. 2. You are banned to use it on the part where you have a scar, eczema, or dermatitis. 3. In case of getting it into your eyes, you have to wash it immediately.

KEEP OUT OF REACH OF CHILDREN

Keep out of reach of babies and children

INDICATIONS & USAGE

Indications & Usage: At the last step of skin care, Apply small spots of Cream over your face, smoothening it out and gently dab till absorbed.

DOSAGE & ADMINISTRATION

Dosage & Administration: Take an adequate amount of this product.